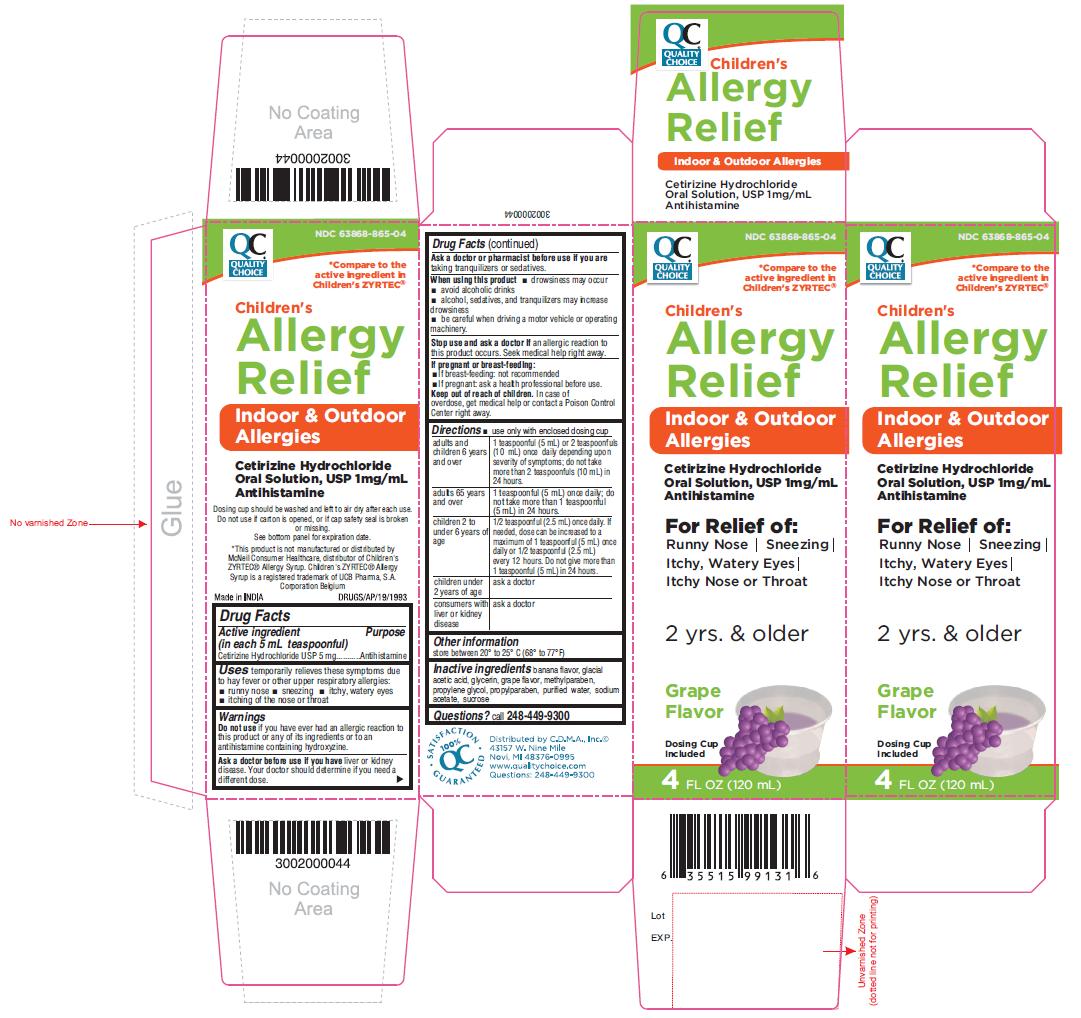 DRUG LABEL: CHILDRENS ALLERGY RELIEF
NDC: 63868-865 | Form: SOLUTION
Manufacturer: C.D.M.A., Inc.
Category: otc | Type: Human OTC Drug Label
Date: 20201213

ACTIVE INGREDIENTS: CETIRIZINE HYDROCHLORIDE 1 mg/1 mL
INACTIVE INGREDIENTS: ACETIC ACID; GLYCERIN; METHYLPARABEN; PROPYLENE GLYCOL; PROPYLPARABEN; WATER; SODIUM ACETATE; SUCROSE

Active ingredient (in each 5 mL teaspoonful)

Cetirizine Hydrochloride USP 5 mg

Purpose

Antihistamine

Uses

temporarily relieves these symptoms due to hay fever or other upper respiratory allergies:

- runny nose
- sneezing
- itchy, watery eyes
- itching of the nose or throat

Warnings

Do not use if you have ever had an allergic reaction to this product or any of its ingredients or to an antihistamine containing hydroxyzine.

Ask a doctor before use if you have

liver or kidney disease. Your doctor should determine if you need a different dose.

Ask a doctor or pharmacist before use if you are

taking tranquilizers or sedatives.

When using this product

- drowsiness may occur
- avoid alcoholic drinks
- alcohol, sedatives, and tranquilizers may increase drowsiness
- be careful when driving a motor vehicle or operating machinery.

Stop use and ask a doctor if

an allergic reaction to this product occurs. Seek medical help right away.

If pregnant or breast-feeding

- If breast-feeding: not recommended
- If pregnant: ask a health professional before use.

Keep out of reach of children.

In case of overdose, get medical help or contact a Poison Control Center right away.

Directions

- use only with enclosed dosing cup

adults and children 6 years and over | 1 teaspoonful (5 mL) or 2 teaspoonfuls (10 mL) once daily depending upon severity of symptoms; do not take more than 2 teaspoonfuls (10 mL) in 24 hours.
adults 65 years and over | 1 teaspoonful (5 mL) once daily; do not take more than 1 teaspoonful (5 mL) in 24 hours.
children 2 to under 6 years of age | 1/2 teaspoonful (2.5 mL) once daily. If needed, dose can be increased to a maximum of 1 teaspoonful (5 mL) once daily or 1/2 teaspoonful (2.5 mL) every 12 hours. Do not give more than 1 teaspoonful (5 mL) in 24 hours.
children under 2 years of age | ask a doctor
consumers with liver or kidney disease | ask a doctor

Other information

store between 20° to 25° C (68° to 77°F)

Inactive ingredients

banana flavor, glacial acetic acid, glycerin, grape flavor, methylparaben, propylene glycol, propylparaben, purified water, sodium acetate, sucrose

Questions?

call 248-449-9300
Distributed by:
C.D.M.A, Inc.©
43157 W.Nine Mile
Novi.MI 48376-0995
www.qualitychoice.com
Questions: 248-449-9300

PACKAGE LABEL- PRINCIPAL DISPLAY PANEL 4 FL OZ (120 mL Bottle)

NDC 63868-865-04
*Compare to the
active ingredient in
Children's ZYRTEC®
Children's
Allergy
Relief
Indoor & Outdoor
Allergies

Cetirizine Hydrochloride
Oral Solution, USP 1mg/mL
Antihistamine
For Relief of:
Runny Nose | Sneezing
Itchy, Watery Eyes |
Itchy Nose or Throat

2 yrs. & older

Grape
Flavor

Dosing Cup
Included

4 FL OZ (120 mL)